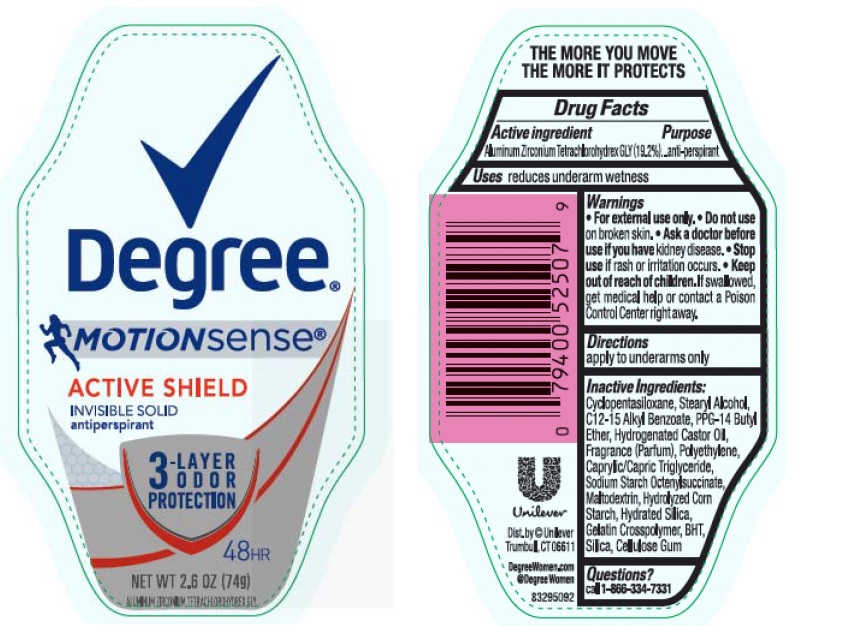 DRUG LABEL: Degree
NDC: 64942-1430 | Form: STICK
Manufacturer: Conopco Inc. d/b/a Unilever
Category: otc | Type: HUMAN OTC DRUG LABEL
Date: 20161012

ACTIVE INGREDIENTS: Aluminum Zirconium Tetrachlorohydrex GLY 19.2 g/100 g
INACTIVE INGREDIENTS: CYCLOMETHICONE 5; STEARYL ALCOHOL; ALKYL (C12-15) BENZOATE; PPG-14 BUTYL ETHER; HYDROGENATED CASTOR OIL; HIGH DENSITY POLYETHYLENE; MEDIUM-CHAIN TRIGLYCERIDES; MALTODEXTRIN; STARCH, CORN; HYDRATED SILICA; BUTYLATED HYDROXYTOLUENE; SILICON DIOXIDE; CARBOXYMETHYLCELLULOSE SODIUM, UNSPECIFIED FORM

Degree MotionSense Active Shield antiperspirant deodorant

Active Ingredient

Aluminum Zirconium Tetrachlorohydrex GLY (19.2%)

Purpose
anti-perspirant

Uses
reduces underarm wetness

Warnings
• For external use only

• Do not use on broken skin

• Ask a doctor before use if you have kidney disease

• Stop use if rash or irritation occurs

• Keep out of reach of children. If swallowed, get medical help or contact a Poison Control Center right away.

Directions

apply to underarms only

INACTIVE INGREDIENT

Inactive ingredients Cyclopentasiloxane, Stearyl Alcohol, C12-15 Alkyl Benzoate, PPG-14 Butyl Ether, Hydrogenated Castor Oil, Fragrance (Parfum), Polyethylene, Caprylic/Capric Triglyceride, Sodium Starch Octenylsuccinate, Maltodextrin, Hydrolyzed Corn Starch, Hydrated Silica, Gelatin Crosspolymer, BHT, Silica, Cellulose Gum

Questions?
Call toll-free 1-866-334-7331